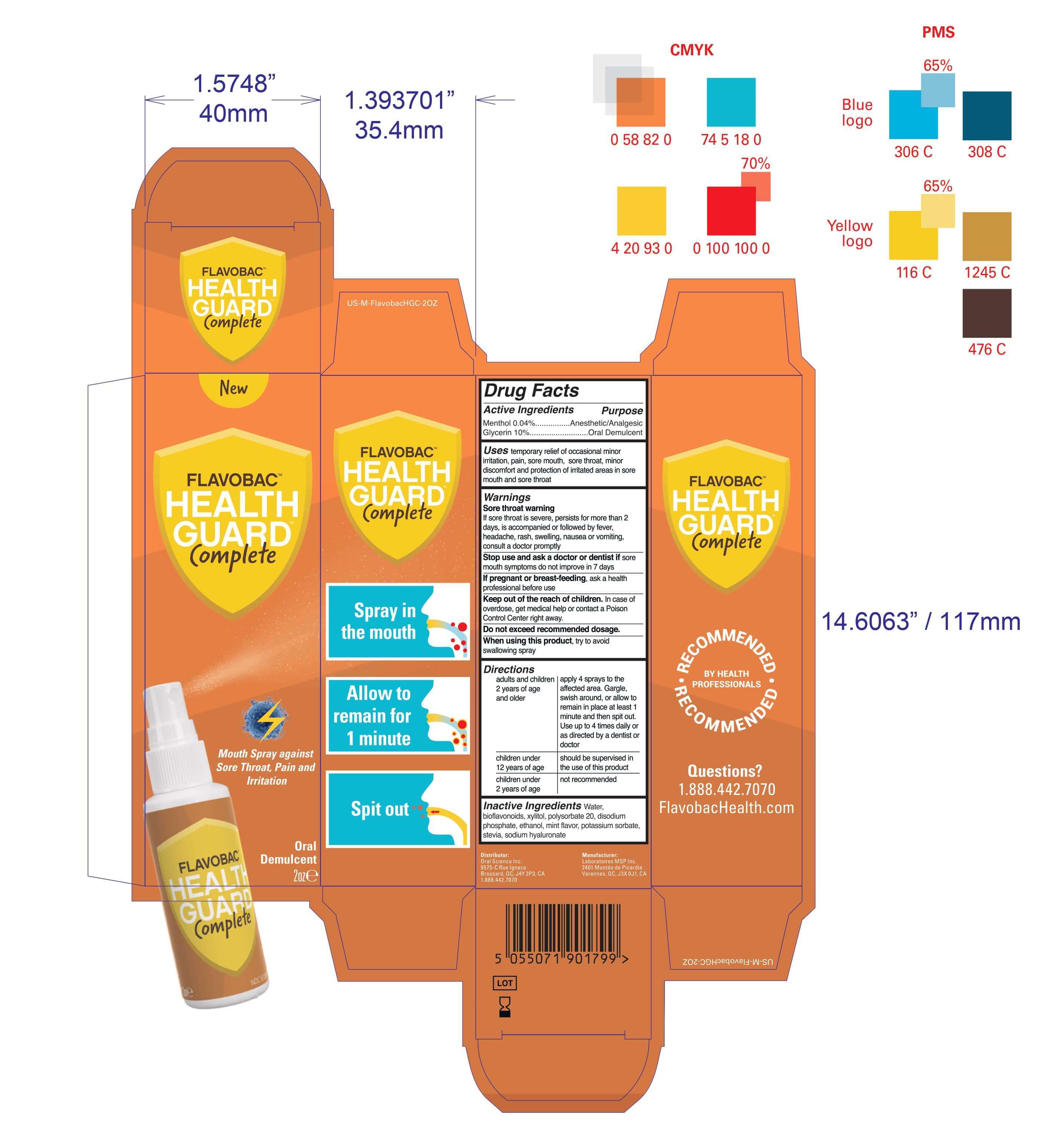 DRUG LABEL: Flavobac Health Guard Complete
NDC: 81359-111 | Form: SPRAY
Manufacturer: Oral Science Inc
Category: otc | Type: HUMAN OTC DRUG LABEL
Date: 20221029

ACTIVE INGREDIENTS: MENTHOL 0.04 mg/100 mL; GLYCERIN 10 mg/100 mL
INACTIVE INGREDIENTS: POTASSIUM SORBATE; XYLITOL; POLYSORBATE 20; SODIUM PHOSPHATE, DIBASIC, ANHYDROUS; STEVIA LEAF; ALCOHOL; MINT; CITRUS BIOFLAVONOIDS; WATER; HYALURONATE SODIUM

Oral Science-ColdFlu Spray

Active Ingredient(s)

Menthol 0.04%................Anesthetic/Analgesic

Glycerin 10%...........................Oral Demulcent

Purpose

Anesthetic/Analgesic

Oral Demulcent

Use

temporary relief of occasional minor irritation, pain, sore mouth, sore throat, minor discomfort and protection of irritated areas in sore mouth and sore throat

Warnings

Sore throat warning

If sore throat is severe, persists for more than 2 days, is accompanied or followed by fever, headache, rash, swelling, nausea or vomiting, consult a doctor promptly

Stop use and ask a doctor or dentist if sore mouth symptoms do not improve in 7 days
If pregnant or breast-feeding, ask a health professional before use

Keep out of the reach of children.

In case of overdose, get medical help or contact a Poison Control Center right away.

Do not exceed the recommended dosage. When using this product, try to avoid swallowing spray

WHEN USING

try to avoid swallowing spray

PREGNANCY

If pregnant or breast-feeding, ask a health professional before use

OTHER SAFETY INFORMATION

Do not exceed the recommended dosage.

STOP USE

sore mouth symptoms do not improve in 7 days

Keep out of reach of children. If swallowed, get medical help or contact a Poison Control Center right away.

Directions

For adults and children 2 years of age and older: apply 4 sprays to the affected area. Gargle, swish around, or allow to remain in place at least 1 minute and then spit it out. Use up to 4 times daily or as directed by a dentist or doctor

children under 12 years of age: should be supervised in the use of this product

children under 2 years of age: not recommended

Inactive ingredients

purified Water, bioflavonoids, xylitol, polysorbate 20, disodium phosphate, ethanol, mint flavor, potassium sorbate, stevia, sodium hyaluronate

Package Label - Principal Display Panel

59 mL NDC: 81359-111-11